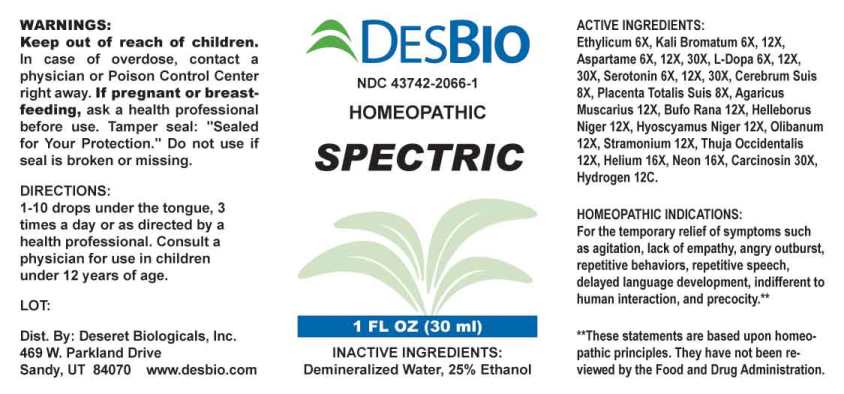 DRUG LABEL: Spectric
NDC: 43742-2066 | Form: LIQUID
Manufacturer: Deseret Biologicals, Inc
Category: homeopathic | Type: HUMAN OTC DRUG LABEL
Date: 20240911

ACTIVE INGREDIENTS: ALCOHOL 6 [hp_X]/1 mL; POTASSIUM BROMIDE 6 [hp_X]/1 mL; ASPARTAME 6 [hp_X]/1 mL; LEVODOPA 6 [hp_X]/1 mL; SEROTONIN HYDROCHLORIDE 6 [hp_X]/1 mL; SUS SCROFA CEREBRUM 8 [hp_X]/1 mL; SUS SCROFA PLACENTA 8 [hp_X]/1 mL; AMANITA MUSCARIA WHOLE 12 [hp_X]/1 mL; BUFO BUFO CUTANEOUS GLAND 12 [hp_X]/1 mL; HELLEBORUS NIGER ROOT 12 [hp_X]/1 mL; HYOSCYAMUS NIGER 12 [hp_X]/1 mL; INDIAN FRANKINCENSE 12 [hp_X]/1 mL; DATURA STRAMONIUM 12 [hp_X]/1 mL; THUJA OCCIDENTALIS LEAFY TWIG 12 [hp_X]/1 mL; HELIUM 16 [hp_X]/1 mL; NEON 16 [hp_X]/1 mL; HUMAN BREAST TUMOR CELL 30 [hp_X]/1 mL; HYDROGEN 12 [hp_C]/1 mL
INACTIVE INGREDIENTS: WATER

DRUG FACTS:

ACTIVE INGREDIENTS:

Ethylicum 6X, Kali Bromatum 6X, 12X, Aspartame 6X, 12X, 30X, L-Dopa 6X, 12X, 30X, Serotonin (Hydrochloride) 6X, 12X, 30X, Cerebrum Suis 8X, Placenta Totalis Suis 8X, Agaricus Muscarius 12X, Bufo Rana 12X, Helleborus Niger 12X, Hyoscyamus Niger 12X, Olibanum (Boswellia Serrata) 12X, Stramonium 12X, Thuja Occidentalis 12X, Helium 16X, Neon 16X, Carcinosin 30X, Hydrogen 12C.

HOMEOPATHIC INDICATIONS:

For the temporary relief of symptoms such as agitation, lack of empathy, angry outburst, repetitive behaviors, repetitive speech, delayed language development, indifferent to human interaction, and precocity.**

**These statements are based upon homeopathic principles. They have not been reviewed by the Food and Drug Administration.

WARNINGS:

Keep out of reach of children. In case of overdose, contact a physician or Poison Control Center right away.

If pregnant or breast-feeding, ask a health professional before use.

Tamper seal: "Sealed for Your Protection." Do not use if seal is broken or missing.

Keep out of reach of children. In case of overdose, contact a physician or Poison Control Center right away.

DIRECTIONS:

1-10 drops under the tongue, 3 times a day or as directed by a health professional. Consult a physician for use in children under 12 years of age.

HOMEOPATHIC INDICATIONS:

For the temporary relief of symptoms such as agitation, lack of empathy, angry outburst, repetitive behaviors, repetitive speech, delayed language development, indifferent to human interaction, and precocity.**

**These statements are based upon homeopathic principles. They have not been reviewed by the Food and Drug Administration.

INACTIVE INGREDIENTS:

Demineralized Water, 25% Ethanol

QUESTIONS:

Dist. By: Deseret Biologicals, Inc.
469 W. Parkland Drive
Sandy, UT 84070 www.desbio.com

PACKAGE LABEL DISPLAY:

DESBIO
NDC 43742-2066-1
HOMEOPATHIC
SPECTRIC

1 FL OZ (30 ml)